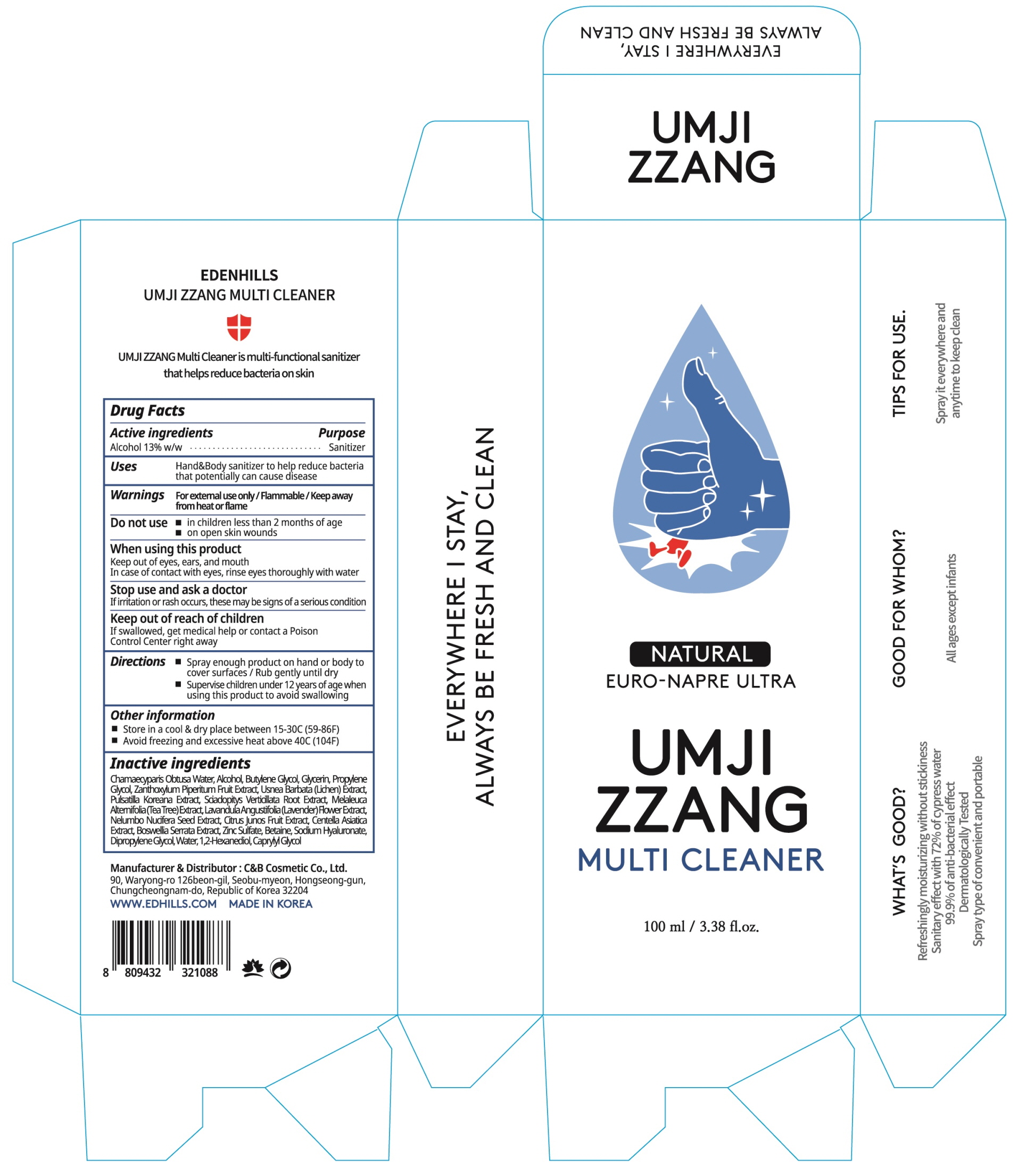 DRUG LABEL: Edenhills Umjizzang Multi Cleaner
NDC: 60611-0110 | Form: SPRAY
Manufacturer: C&BCOSMETIC Co., Ltd.
Category: otc | Type: HUMAN OTC DRUG LABEL
Date: 20200805

ACTIVE INGREDIENTS: ALCOHOL 13 mL/100 mL
INACTIVE INGREDIENTS: CHAMAECYPARIS OBTUSA WOOD OIL; Butylene Glycol; Glycerin; Propylene Glycol; ZANTHOXYLUM PIPERITUM FRUIT PULP; USNEA BARBATA; PULSATILLA CERNUA ROOT; SCIADOPITYS VERTICILLATA ROOT; LAVANDULA ANGUSTIFOLIA SUBSP. ANGUSTIFOLIA FLOWER; NELUMBO NUCIFERA SEED; CITRUS JUNOS FRUIT; CENTELLA ASIATICA WHOLE; INDIAN FRANKINCENSE; ZINC SULFATE, UNSPECIFIED FORM; Betaine; HYALURONATE SODIUM; Dipropylene Glycol; Water; 1,2-Hexanediol; Caprylyl Glycol

ACTIVE INGREDIENT

Alcohol 13% w/w

INACTIVE INGREDIENT

Chamaecyparis Obtusa Water, Butylene Glycol, Glycerin, Propylene Glycol, Zanthoxylum Piperitum Fruit Extract, Usnea Barbata (Lichen) Extract, Pulsatilla Koreana Extract, Sciadopitys Verticillata Root Extract, Melaleuca Alternifolia (Tea Tree) Extract, Lavandula Angustifolia (Lavender) Flower Extract, Nelumbo Nucifera Seed Extract, Citrus Junos Fruit Extract, Centella Asiatica Extract, Boswellia Serrata Extract, Zinc Sulfate, Betaine, Sodium Hyaluronate, Dipropylene Glycol, Water, 1,2-Hexanediol, Caprylyl Glycol

PURPOSE

Sanitizer

WARNINGS

For external use only. Flammable. Keep away from heat or flame
--------------------------------------------------------------------------------------------------------
Do not use
• in children less than 2 months of age
• on open skin wounds
--------------------------------------------------------------------------------------------------------
When using this product keep out of eyes, ears, and mouth. In case of contact with eyes, rinse eyes thoroughly with water.
--------------------------------------------------------------------------------------------------------
Stop use and ask a doctor if irritation or rash occurs. These may be signs of a serious condition.

KEEP OUT OF REACH OF CHILDREN

If swallowed, get medical help or contact a Poison Control Center right away.

Uses

Hand & Body sanitizer to help reduce bacteria that potentially can cause disease.

Directions

• Spray enough product on hand or body to cover surfaces. Rub gently until dry.
• Supervise children under 12 years of age when using this product to avoid swallowing.

Other information

• Store in a cool & dry place between 15-30C (59-86F)
• Avoid freezing and excessive heat above 40C (104F)